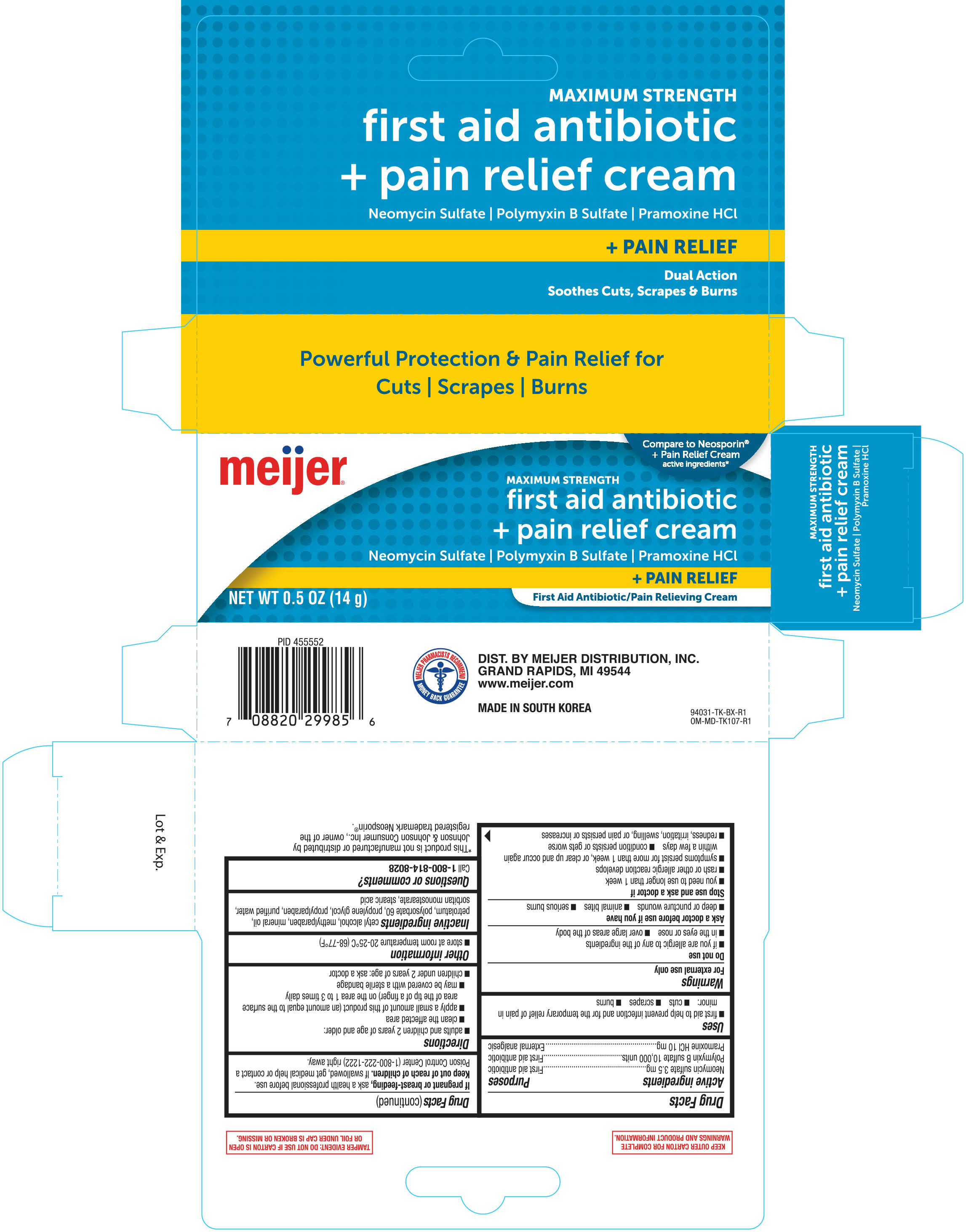 DRUG LABEL: antibiotic plus pain relief
NDC: 41250-960 | Form: CREAM
Manufacturer: Meijer, Inc.
Category: otc | Type: HUMAN OTC DRUG LABEL
Date: 20181218

ACTIVE INGREDIENTS: NEOMYCIN SULFATE 3.5 mg/1 g; POLYMYXIN B SULFATE 10000 [iU]/1 g; PRAMOXINE HYDROCHLORIDE 10 mg/1 g
INACTIVE INGREDIENTS: CETYL ALCOHOL; MINERAL OIL; METHYLPARABEN; PETROLATUM; POLYSORBATE 60; PROPYLENE GLYCOL; PROPYLPARABEN; SORBITAN MONOSTEARATE; STEARIC ACID; WATER

Meijer Antibiotic Plus Pain Relief Cream 0.5oz (94029, 2018)

Active Ingredients Purposes

Neomycin sulfate 3.5 mg.........................First aid antibiotic

Polymyxin B sulfate 10,000 units.............First aid antibiotic

Pramoxine HCl 10 mg..............................External analgesic

Uses

- first aid to help prevent infection and for the temporary relief of pain in minor:
- cuts
- scrapes
- burns

WARNINGS

For external use only

Do not use

- if you are allergic to any of the ingredients
- in the eyes or nose
- over large areas of the body

Ask a doctor before use if you have

- deep or puncture wounds
- animal bites
- serious burns

Stop use and ask a doctor if

- you need to use longer than 1 week
- rash or other allergic reaction develops
- symptoms persist for more than 1 week, or clear up and occur again within a few days
- condition persists or gets worse
- redness, irritation, swelling, or pain persists or increases

PREGNANCY OR BREAST FEEDING

If pregnant or breast-feeding, ask a health professional before use.

Keep out of reach of children. If swallowed, get medical help or contact a Poison Control Center (1-800-222-1222) right away.

Directions

- adults and children 2 years of age and older:
- clean the affected area
- apply a small amount of this product (an amount equal to the surface area of the tip of a finger) on the area 1 to 3 times daily
- may be covered with a sterile bandage
- children under 2 years of age: ask a doctor

Other information

- store at room temperature 20-25°C (68-77°F)

INACTIVE INGREDIENT

cetyl alcohol, methylparaben, mineral oil, petrolatum, polysorbate 60, propylene glycol, propylparaben, purified water, sorbitan monostearate, stearic acid

Questions or comments?

Call 1-800-814-8028

DOSAGE AND ADMINISTRATION

DIST. BY MEIJER DISTRIBUTION, INC.

GRAND RAPIDS, MI 49544

www.meijer.com

MADE IN SOUTH KOREA